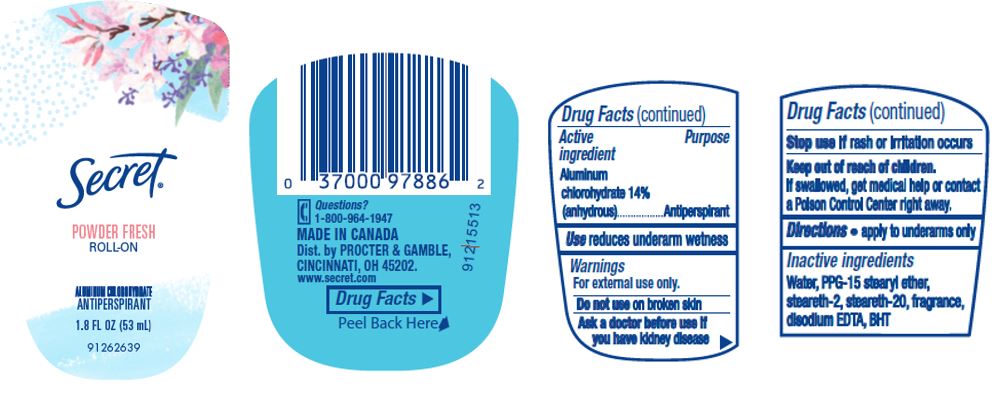 DRUG LABEL: Secret Roll-On
NDC: 37000-135 | Form: LIQUID
Manufacturer: The Procter & Gamble Manufacturing Company
Category: otc | Type: HUMAN OTC DRUG LABEL
Date: 20251218

ACTIVE INGREDIENTS: ALUMINUM CHLOROHYDRATE 14 g/100 mL
INACTIVE INGREDIENTS: WATER; PPG-15 STEARYL ETHER; STEARETH-2; STEARETH-20; EDETATE DISODIUM; BUTYLATED HYDROXYTOLUENE

Secret® Roll-On
Powder Fresh

Drug Facts

Active ingredient

Aluminum chlorohydrate 14% (anhydrous)

Purpose

Antiperspirant

Use

reduces underarm wetness

Warnings

For external use only.

Do not use on broken skin

Ask a doctor before use if you have kidney disease

Stop use if rash or irritation occurs

Keep out of reach of children. If swallowed, get medical help or contact a Poison Control Center right away.

Directions

apply to underarms only

Inactive ingredients

water, PPG-15 stearyl ether, steareth-2, steareth-20, fragrance, disodium EDTA, BHT

Questions?

1-800-964-1947

Dist. by
PROCTER & GAMBLE,
CINCINNATI, OH
45202.

PRINCIPAL DISPLAY PANEL - 53 mL Canister Label

ROLL-ON

Secret®
powder fresh

Aluminum chlorohydrate
ANTIPERSPIRANT/DEODORANT

Net Wt. 1.8 FL. OZ. (53 mL)